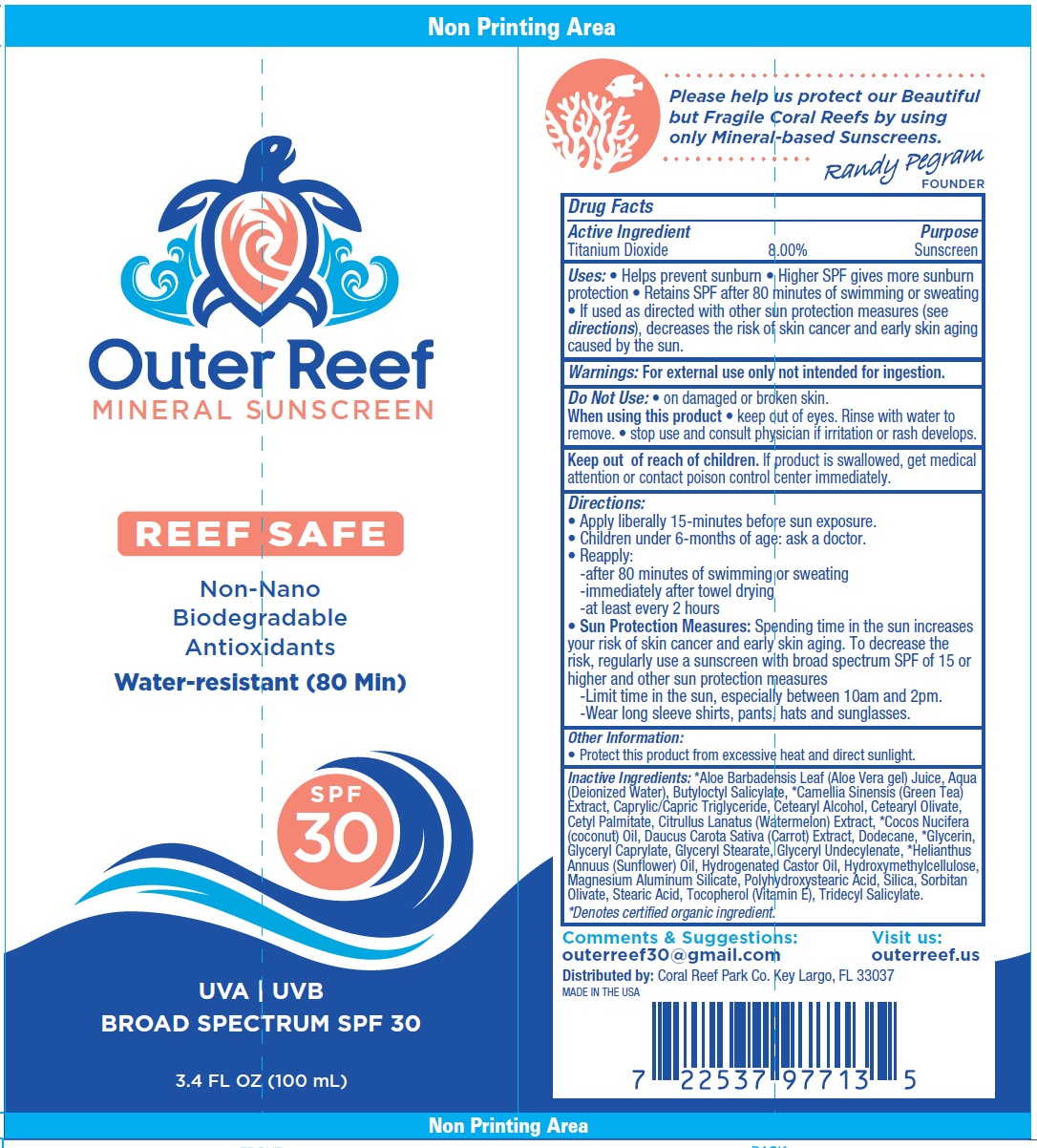 DRUG LABEL: OUTER REEF MINERAL SUNSCREEN SPF 30
NDC: 73691-047 | Form: CREAM
Manufacturer: Coral Reef Park Co., Inc.
Category: otc | Type: HUMAN OTC DRUG LABEL
Date: 20260119

ACTIVE INGREDIENTS: TITANIUM DIOXIDE 80 mg/1 mL
INACTIVE INGREDIENTS: ALOE VERA LEAF; WATER; BUTYLOCTYL SALICYLATE; GREEN TEA LEAF; MEDIUM-CHAIN TRIGLYCERIDES; CETOSTEARYL ALCOHOL; CETEARYL OLIVATE; CETYL PALMITATE; WATERMELON; COCONUT OIL; CARROT; DODECANE; GLYCERIN; GLYCERYL CAPRYLATE; GLYCERYL MONOSTEARATE; GLYCERYL 1-UNDECYLENATE; HELIANTHUS ANNUUS FLOWERING TOP; HYDROGENATED CASTOR OIL; HYDROXYMETHYL CELLULOSE; MAGNESIUM ALUMINUM SILICATE; SILICON DIOXIDE; SORBITAN OLIVATE; STEARIC ACID; TOCOPHEROL; TRIDECYL SALICYLATE

OUTER REEF MINERAL SUNSCREEN SPF 30

Active Ingredient

Titanium Dioxide 8.00%

Purpose

Sunscreen

Uses:

• Helps prevent sunburn • Higher SPF gives more sunburn protection • Retains SPF after 80 minutes of swimming or sweating • If used as directed with other sun protection measures (see directions), decreases the risk of skin cancer and early skin aging caused by the sun.

Warnings:

For external use only not intended for ingestion.

Do Not Use:

• on damaged or broken skin.

When using this product

keep out of eyes. Rinse with water to remove. • stop use and consult physician if irritation or rash develops.

Keep out of reach of children.

If product is swallowed, get medical attention or contact poison control center immediately.

Directions:

• Apply liberally 15-minutes before sun exposure. • Children under 6-months of age: ask a doctor. • Reapply: -after 80 minutes of swimming or sweating -immediately after towel drying -at least every 2 hours • Spending time in the sun increases your risk of skin cancer and early skin aging. To decrease the risk, regularly use a sunscreen with broad spectrum SPF of 15 or higher and other sun protection measures -Limit time in the sun, especially between 10am and 2pm. -Wear long sleeve shirts, pants, hats and sunglasses.
Sun Protection Measures:

Other Information:

• Protect this product from excessive heat and direct sunlight.

Inactive Ingredients:

*Aloe Barbadensis Leaf (Aloe Vera gel) Juice, Aqua (Deionized Water), Butyloctyl Salicylate, *Camellia Sinensis (Green Tea) Extract, Caprylic/Capric Triglyceride, Cetearyl Alcohol, Cetearyl Olivate, Cetyl Palmitate, Citrullus Lanatus (Watermelon) Extract, *Cocos Nucifera (coconut) Oil, Daucus Carota Sativa (Carrot) Extract, Dodecane, *Glycerin, Glyceryl Caprylate, Glyceryl Stearate, Glyceryl Undecylenate, *Helianthus Annuus (Sunflower) Oil, Hydrogenated Castor Oil, Hydroxymethylcellulose, Magnesium Aluminum Silicate, Polyhydroxystearic Acid, Silica, Sorbitan Olivate, Stearic Acid, Tocopherol (Vitamin E), Tridecyl Salicylate. *Denotes certified organic ingredient.